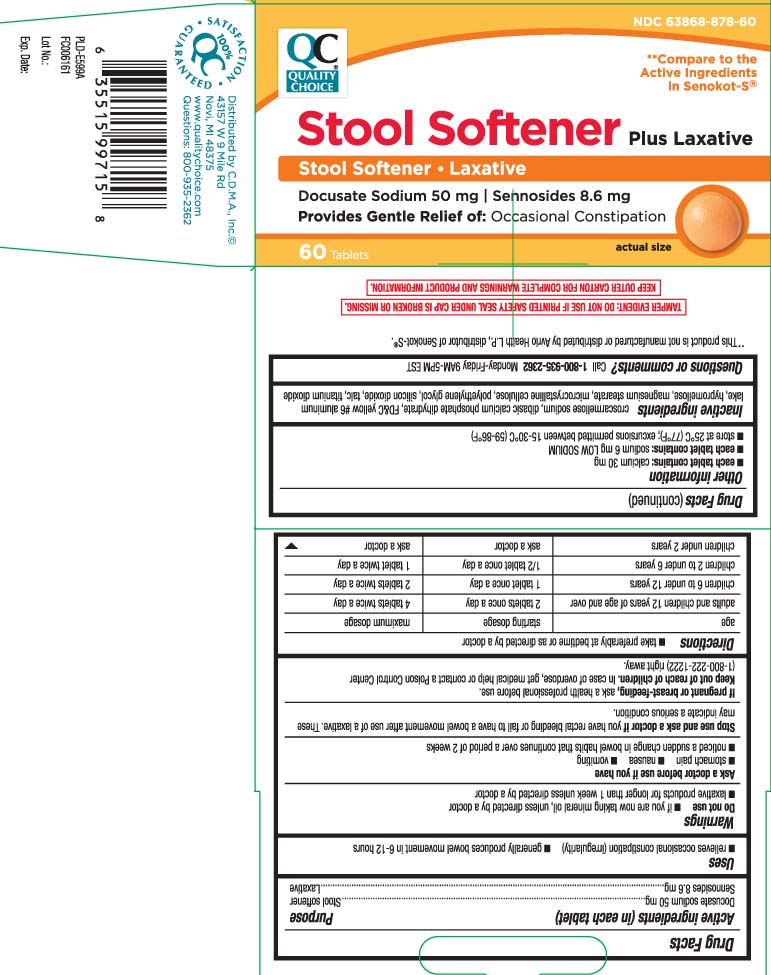 DRUG LABEL: Stool Softener plus Laxative
NDC: 63868-878 | Form: TABLET
Manufacturer: QUALITY CHOICE (Chain Drug Marketing Association)
Category: otc | Type: HUMAN OTC DRUG LABEL
Date: 20240809

ACTIVE INGREDIENTS: DOCUSATE SODIUM 50 mg/1 1; SENNOSIDES 8.6 mg/1 1
INACTIVE INGREDIENTS: CROSCARMELLOSE SODIUM; DIBASIC CALCIUM PHOSPHATE DIHYDRATE; FD&C YELLOW NO. 6; HYPROMELLOSES; MAGNESIUM STEARATE; CELLULOSE, MICROCRYSTALLINE; POLYETHYLENE GLYCOL, UNSPECIFIED; SILICON DIOXIDE; TALC; TITANIUM DIOXIDE

DRUG FACTS

Active Ingredients (in each tablet)

Docusate Sodium 50 mg
Sennosides 8.6 mg

Purpose

Stool softener

Laxative

Purpose

Stool softener

laxative

Uses

- relieves occasional constipation (irregularity)
- generally causes bowel movement in 6- 12 hours.

Warnings

Do not use

- If you are now taking mineral oil, unless directed by a doctor
- laxative products for longer than 1 week unless directed by a doctor

Ask a doctor before use if you have

- stomach pain
- nausea
- vomiting
- noticed a sudden change in bowel habits that continues over a period of 2 weeks.

Stop use and ask a doctor if

- you have rectal bleeding or fail to have a bowel movement after use of a laxative. These may indicate a serious condition.

If pregnant or breastfeeding,

ask a health professional before use.

Keep out of reach of children.

In case of overdose, get medical help or contact a Poison Control Center (1-800-222-1222) right away.

Directions

- Take preferably at bedtime or as directed by a doctor

age | starting dosage | maximum dosage
adults and children 12 years of age and older | 2 tablets once a day | 4 tablets twice a day
children 6 to under 12 years | 1 tablet once a day | 2 tablets twice a day
children 2 to under 6 years | 1/2 tablet once a day | 1 tablet twice a day
children under 2 years | ask a doctor | ask a doctor

Other information

- each tablet contains: calcium 30 mg
- each tablet contains: sodium 6 mg LOW SODIUM
- store at 25ºC (77º); excursions permitted between 15º-30ºC (59º-86ºF)

Inactive Ingredients

croscarmellose sodium, dibasic calcium phosphate dihydrate, FD&C yellow #6 aluminum lake, hypromellose, magnesium stearate, microcrystalline cellulose, polyethylene glycol, silicon dioxide, talc, titanium dioxide.

Questions or comments?

call 1-800-935-2362 Monday-Friday 9AM-5PM EST

Principal Display Panel

**Compare to the Active Ingredients in Senokot-S®

Stool Softener Plus Laxative

Stool Softener • Laxative

Docusate Sodium, 50 mg | Sennosides, 8.6 mg
Provides Gentle Relief of: Occasional Constipation

Tablets

†This product is not manufactured or distributed by Avrio Health L.P., distributor of Senokot-S®

TAMPER EVIDENT: DO NOT USE IF PRINTED SAFETY SEAL UNDER CAP ID BROKEN OR MISSING.

KEEP OUTER CARTON FOR COMPLETE WARNINGS AND PRODUCT INFORMATION.

Distributed by C.D.M.A., Inc©

43157 W. 9 Mile Rd

Novi, MI 48376-0995

www.qualitychoice.com

Product Label

QUALITY CHOICE Stool Softener